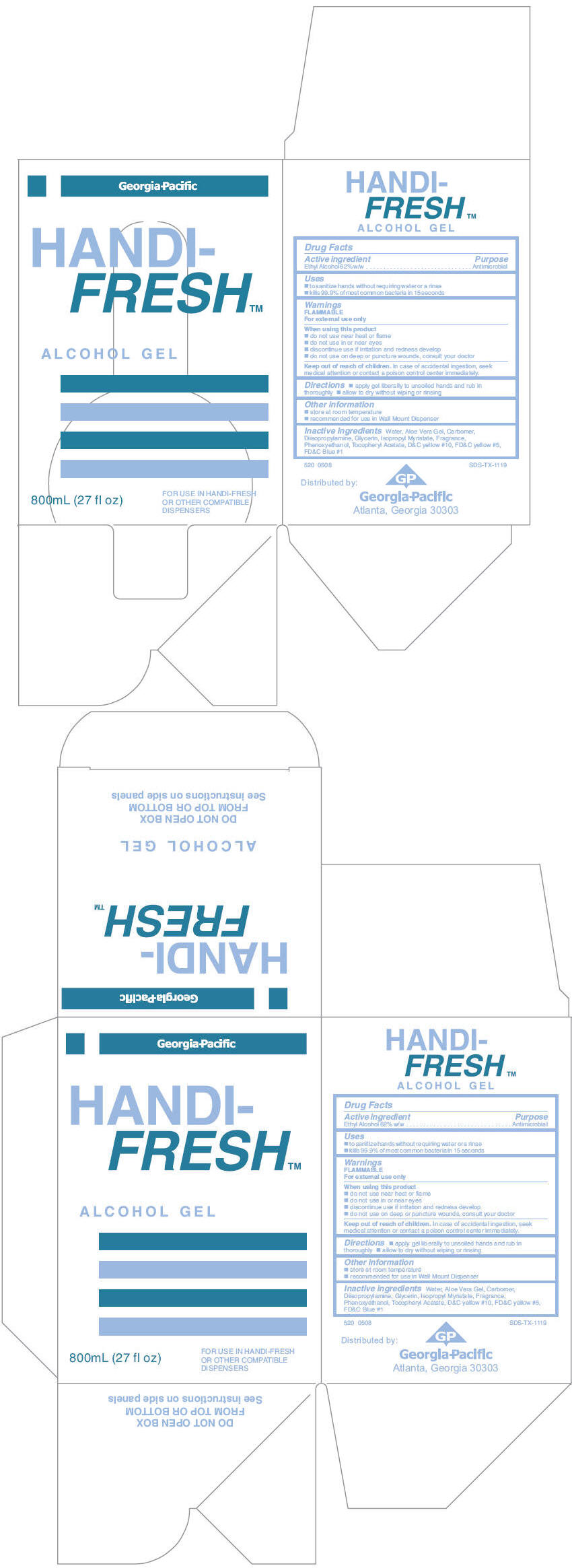 DRUG LABEL: Georgia-Pacific Alcohol Hand Sanitizer
NDC: 54622-520 | Form: SOAP
Manufacturer: Georgia-Pacific Consumer Products LP
Category: otc | Type: HUMAN OTC DRUG LABEL
Date: 20180125

ACTIVE INGREDIENTS: ALCOHOL 0.67 mL/1 mL
INACTIVE INGREDIENTS: WATER; CARBOMER HOMOPOLYMER TYPE C (ALLYL PENTAERYTHRITOL CROSSLINKED); GLYCERIN; ALOE VERA LEAF; ISOPROPYL MYRISTATE; PHENOXYETHANOL; .ALPHA.-TOCOPHEROL ACETATE; DIISOPROPYLAMINE

Georgia-Pacific Alcohol Gel Hand Sanitizer

Drug Facts

Active ingredient

Ethyl Alcohol 62% w/w

Purpose

Antimicrobial

Uses

- to sanitize hands without requiring water or a rinse
- kills 99.9% of most common bacteria in 15 seconds

Warnings

FLAMMABLE

For external use only

When using this product

- do not use near heat or flame
- do not use in or near eyes
- discontinue use if irritation and redness develop
- do not use on deep or puncture wounds, consult your doctor

Keep out of reach of children. In case of accidental ingestion, seek medical attention or contact a poison control center immediately.

Directions

- apply gel liberally to unsoiled hands and rub in thoroughly
- allow to dry without wiping or rinsing

Other information

- store at room temperature
- recommended for use in Wall Mount Dispenser

Inactive ingredients

Water, Aloe Vera Gel, Carbomer, Diisopropylamine, Glycerin, Isopropyl Myristate, Fragrance, Phenoxyethanol, Tocopheryl Acetate, D&C yellow #10, FD&C yellow #5, FD&C Blue #1

Distributed by:
Georgia-Pacific
Atlanta, Georgia 30303

PRINCIPAL DISPLAY PANEL - 800 mL Bag Carton

Georgia-Pacific

HANDI-
FRESH™

ALCOHOL GEL

800mL (27 fl oz)

FOR USE IN HANDI-FRESH
OR OTHER COMPATIBLE
DISPENSERS